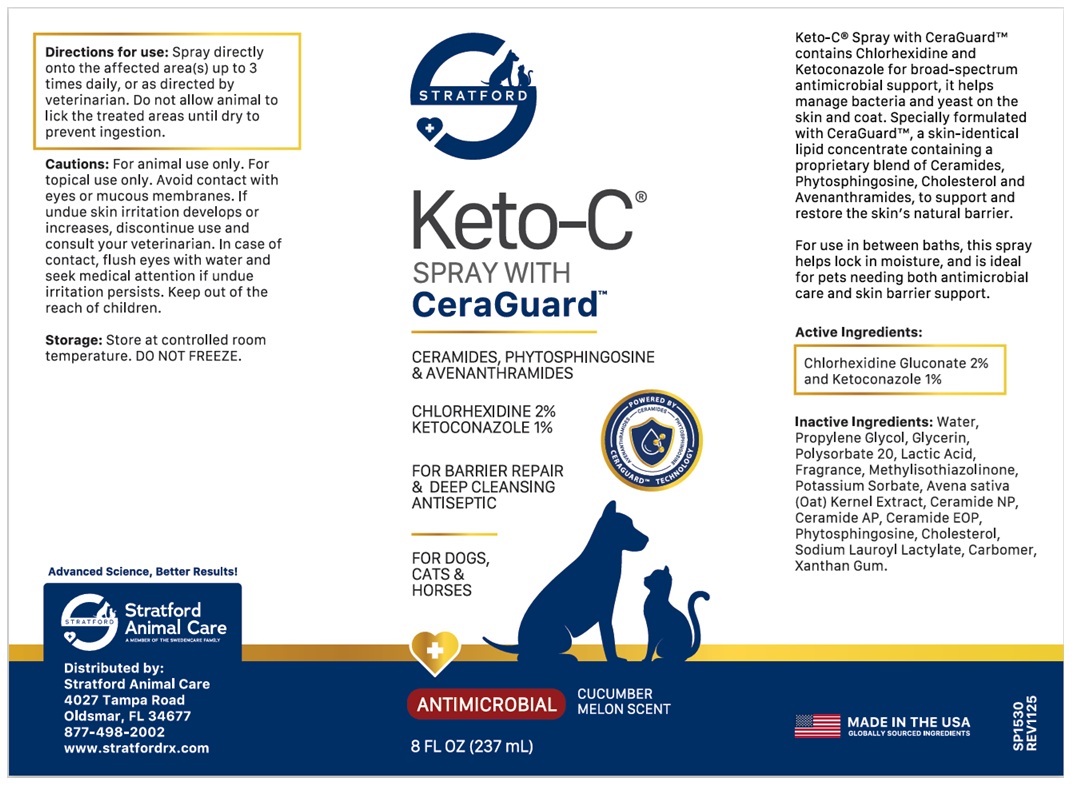 DRUG LABEL: STRATFORD Keto-C WITH CeraGuard
NDC: 86069-138 | Form: SPRAY
Manufacturer: Stratford Care Usa, Inc.
Category: animal | Type: OTC ANIMAL DRUG LABEL
Date: 20260204

ACTIVE INGREDIENTS: CHLORHEXIDINE GLUCONATE 2 g/100 mL; KETOCONAZOLE 1 g/100 mL
INACTIVE INGREDIENTS: WATER; PROPYLENE GLYCOL; GLYCERIN; POLYSORBATE 20; LACTIC ACID, UNSPECIFIED FORM; METHYLISOTHIAZOLINONE; POTASSIUM SORBATE; OAT; CERAMIDE NP; CERAMIDE AP; CERAMIDE 9; PHYTOSPHINGOSINE; CHOLESTEROL; SODIUM LAUROYL LACTYLATE; CARBOMER HOMOPOLYMER, UNSPECIFIED TYPE; XANTHAN GUM

STRATFORD Keto-C® SPRAY WITH CeraGuardTM

Keto-C® Spray with CeraGuard™ contains Chlorhexidine and Ketoconazole for broad-spectrum antimicrobial support, it helps manage bacteria and yeast on the skin and coat. Specially formulated with CeraGuard™, a skin-identical lipid concentrate containing a proprietary blend of Ceramides, Phytosphingosine, Cholesterol and Avenanthramides, to support and restore the skin’s natural barrier.

For use in between baths, this spray helps lock in moisture, and is ideal for pets needing both antimicrobial care and skin barrier support.

Active Ingredients:

Chlorhexidine Gluconate 2% and Ketoconazole 1%

Inactive Ingredients:

Water, Propylene Glycol, Glycerin, Polysorbate 20, Lactic Acid, Fragrance, Methylisothiazolinone, Potassium Sorbate, Avena sativa (Oat) Kernel Extract, Ceramide NP, Ceramide AP, Ceramide EOP, Phytosphingosine, Cholesterol, Sodium Lauroyl Lactylate, Carbomer, Xanthan Gum.

Directions for use:

Spray directly onto the affected area(s) up to 3 times daily, or as directed by veterinarian. Do not allow animal to lick the treated areas until dry to prevent ingestion.

Cautions:

For animal use only. For topical use only. Avoid contact with eyes or mucous membranes. If undue skin irritation develops or increases, discontinue use and consult your veterinarian. In case of contact, flush eyes with water and seek medical attention if undue irritation persists. Keep out of the reach of children.

Storage:

Store at controlled room temperature. DO NOT FREEZE.

CERAMIDES, PHYTOSPHINGOSINE & AVENANTHRAMIDES

FOR BARRIER REPAIR & DEEP CLEANSING ANTISEPTIC

FOR DOGS, CATS & HORSES

ANTIMICROBIAL

CUCUMBER MELON SCENT

MADE IN THE USA
GLOBALLY SOURCED INGREDIENTS

Advanced Science, Better Results!

Stratford Animal Care
A MEMBER OF THE SWEDENCARE FAMILY

Distributed by:
Stratford Animal Care
4027 Tampa Road,
Oldsmar, FL 34677
877-498-2002
www.stratfordrx.com